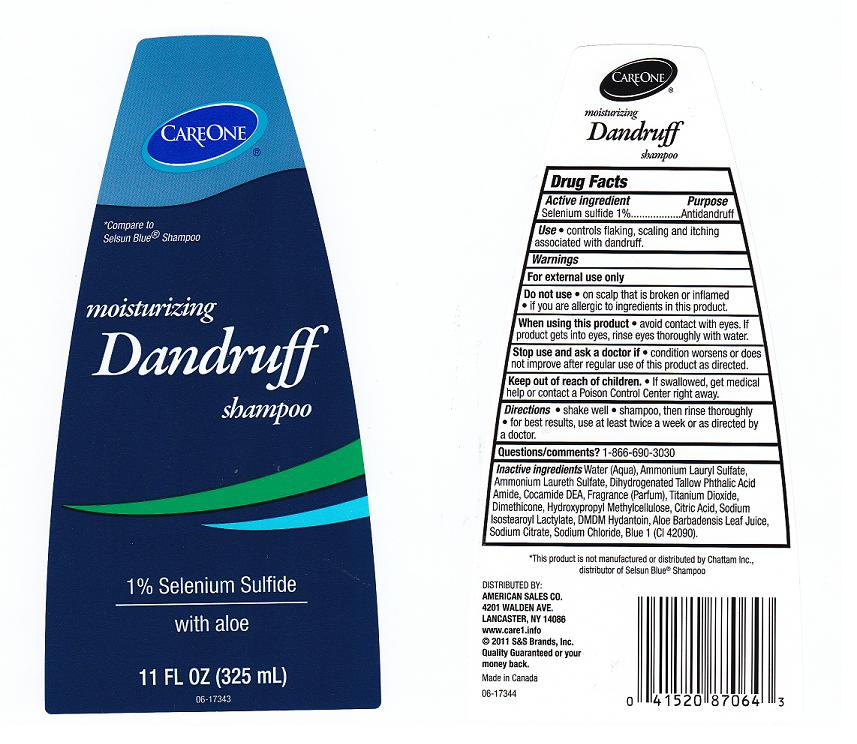 DRUG LABEL: Careone
NDC: 41520-611 | Form: SHAMPOO
Manufacturer: American Sales Company
Category: otc | Type: HUMAN OTC DRUG LABEL
Date: 20110819

ACTIVE INGREDIENTS: SELENIUM SULFIDE 1 mL/100 mL
INACTIVE INGREDIENTS: WATER; AMMONIUM LAURYL SULFATE; AMMONIUM LAURETH-2 SULFATE; COCO DIETHANOLAMIDE; TITANIUM DIOXIDE; DIMETHICONE; HYPROMELLOSES; CITRIC ACID MONOHYDRATE; SODIUM ISOSTEAROYL LACTYLATE; DMDM HYDANTOIN; ALOE VERA LEAF; SODIUM CITRATE; SODIUM CHLORIDE; FD&C BLUE NO. 1; DIHYDROGENATED TALLOW PHTHALIC ACID AMIDE

Active Ingredient

Selenium Sulfide 1%

Purpose

Anti-Dandruff

Uses

Controls flaking, scaling and itching associated with dandruff.

Warnings

For external use only

Do not use

- on scalp that is broken or inflamed
- if you are allergic to ingredients in this product

When using this product

avoid contact with eyes. If product gets into eyes, rinse eyes thoroughly with water.

Stop using this product and ask a doctor if

condition worsens or does not improve after regular use of this product as directed

Keep out of reach of children

If swallowed, get medical help or contact a Poison Control Center right away.

Directions

- shake well
- shampoo, then rinse thoroughly
- for best results, use at least twice a week or as directed by a doctor

Questions? Comments?

1 - 877 - 932 - 7948

Inactive Ingredients

Water (Aqua), Ammonium Lauryl Sulfate, Ammonium Laureth Sulfate, Dihydrogenated Tallow Phthalic Acid Amide, Cocamide DEA, Fragrance (Parfum), Titanium Dioxide, Dimethicone, Hydroxypropyl Methylcellulose, Citric Acid, Sodium Isostearoyl Lactylate, DMDM Hydantoin, Aloe Barbadensis Leaf Juice, Sodium Citrate, Sodium Chloride, Blue 1 (CI 42090)